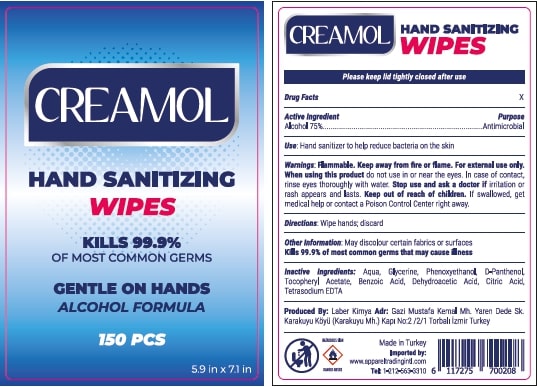 DRUG LABEL: CREAMOL HAND SANITIZING WIPES 150 pcs
NDC: 77892-0011 | Form: SWAB
Manufacturer: LABER KIMYA AR-GE SANAYI TICARET - LEVENT KAHRIMAN
Category: otc | Type: HUMAN OTC DRUG LABEL
Date: 20200907

ACTIVE INGREDIENTS: BENZALKONIUM CHLORIDE 0.13 g/100 g; ALCOHOL 45 g/100 g; ISOPROPYL ALCOHOL 30 g/100 g
INACTIVE INGREDIENTS: PANTHENOL; GLYCERIN; .ALPHA.-TOCOPHEROL, D-; WATER

CREAMOL HAND SANITIZING WIPE 150 pcs

ACTIVE INGREDIENT

Alcohol: 75% (w/w) Purpose: Antimicrobial

PURPOSE

Antimicrobial

Directions

Wipe hands, discard

INDICATIONS AND USAGE

Hand santizer to help reduce bacteria on skin. Kills 99.9% of most common germs that may cause illness.

WARNINGS

For external use only. Flammable, keep away from fire and flame.

Do not use on open wounds, in or near the eyes and in children less than 2 months of age.

WHEN USING

Keep out of eyes, ears, and mouth. In case of contact with eyes, rinse eyes throughly with water.

STOP USE

If irritation and redness develops and persist and in case of poisoning stop use and ask a doctor. Symptoms of Poisoning are dizziness, loss of consciousness and speech disorder.

Keep out of reach of children. If swallowed, get medical help or contact a Poison Control Center right away.

INACTIVE INGREDIENT

ısopropyl alcohol, glycerine, alpha-tocopherol, panthenol, water

Other informations

Store between 15-30 ºC. Avoid freezing and excessive heat above 40ºC